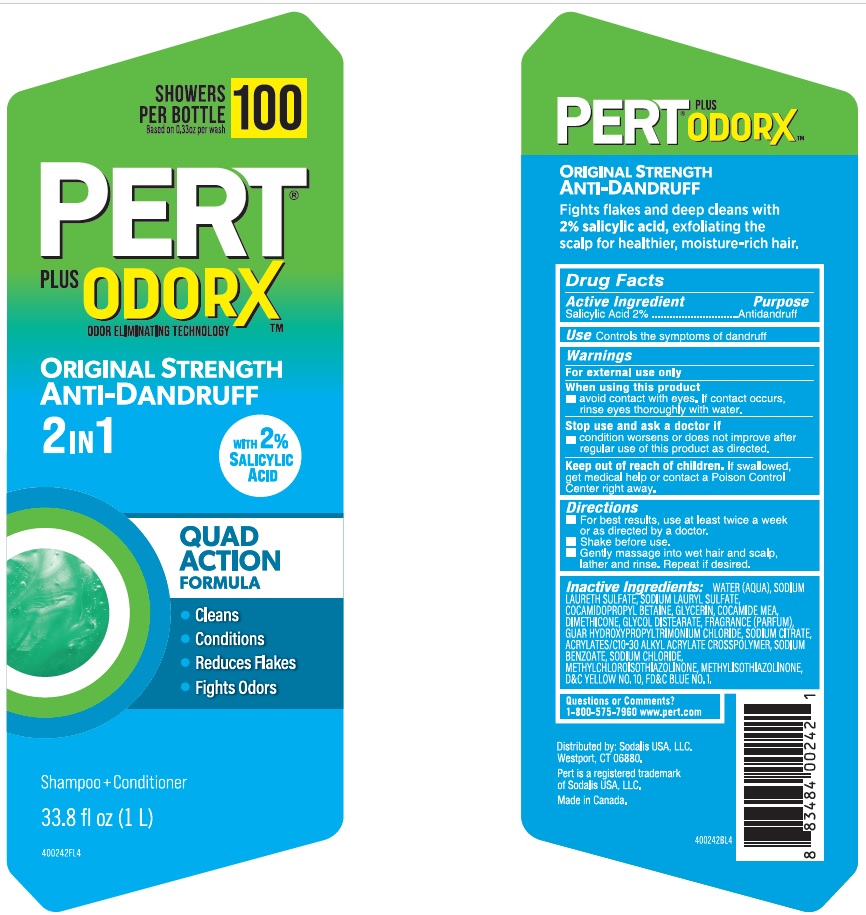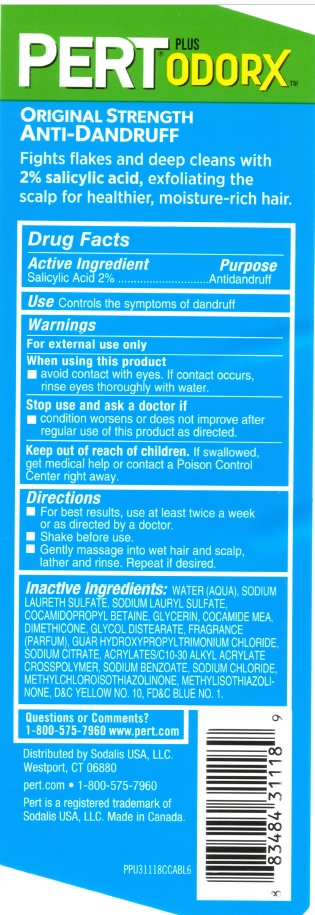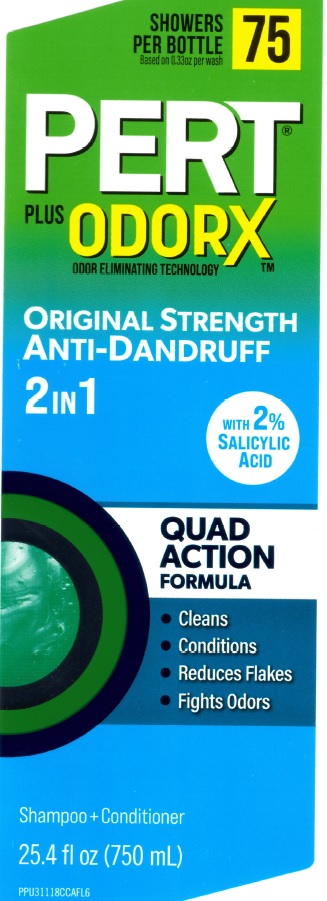 DRUG LABEL: Pert 2 in 1
NDC: 81277-802 | Form: SHAMPOO
Manufacturer: Sodalis USA, LLC
Category: otc | Type: HUMAN OTC DRUG LABEL
Date: 20250813

ACTIVE INGREDIENTS: SALICYLIC ACID 2 g/100 mL
INACTIVE INGREDIENTS: GUAR HYDROXYPROPYLTRIMONIUM CHLORIDE (1.7 SUBSTITUENTS PER SACCHARIDE); ACRYLATES/C10-30 ALKYL ACRYLATE CROSSPOLYMER (60000 MPA.S); GLYCERIN; COCO MONOETHANOLAMIDE; GLYCOL DISTEARATE; SODIUM CITRATE; WATER; DIMETHICONE; SODIUM BENZOATE; SODIUM CHLORIDE; D&C YELLOW NO. 10; COCAMIDOPROPYL BETAINE; FD&C BLUE NO. 1; SODIUM LAURETH SULFATE; METHYLISOTHIAZOLINONE; SODIUM LAURYL SULFATE; METHYLCHLOROISOTHIAZOLINONE

Pert 2 in 1 Advanced+ Anti-Dandruff Shampoo + Conditioner + Salicylic Acid

Active ingredient

Salicylic Acid 2%

Purpose

Antidandruff

INDICATIONS AND USAGE

Use Controls the symptoms of dandruff

Warnings

For external use only

When using this product

- avoid contact with eyes. If contact occurs, rinse eyes thoroughly with water.

Stop use and ask a doctor if

condition worsens or does not improve after regular use of this product as directed.

Keep out of reach of children. If swallowed, get medical help or contact a Poison Control Center right away.

Directions

- For best results, use at least twice a week or as directed by a doctor
- Shake before use.
- Gently massage into wet hair and scalp, lather and rinse. Repeat if desired.

INACTIVE INGREDIENT

Inactive ingredients: Water (Aqua), Sodium Laureth Sulfate, Sodium Lauryl Sulfate, Cocamidopropyl Betaine, Glycerin, Cocamide MEA, Dimethicone, Glycol Distearate, Fragrance (Parfum), Guar Hydroxypropyltrimonium Chloride, Sodium Citrate, Acrylates/C10-30 Alkyl Acrylate Crosspolymer, Sodium Benzoate, Sodium Chloride, Methylchloroisothiazolinone, Methylisothiazolinone, Yellow 10 (CI47005), Blue 1 (CI42090).

Questions or Comments?

1-800-575-7960 www.pert.com

PERT®

2IN1 ADVANCED+

- 2% Salicylic Acid
- Helps Control Dandruff
- Fast-Acting

Distributed by: Sodalis USA, LLC

Westport, CT 06880

Made in Canada.

PACKAGE LABEL

PERT®

PLUS ODORX™

ODOR ELIMINATING TECHNOLOGY

ORIGINAL STRENGTH

ANTI-DANDRUFF

2 IN 1

with 2% SALICYLIC ACID

QUAD ACTION FORMULA

- Cleans
- Conditions
- Reduces Flakes
- Fights Odors

Shampoo+Conditioner

24.5 fl oz (750 mL)